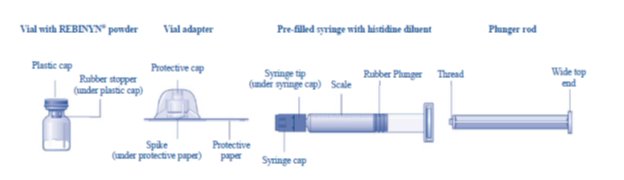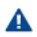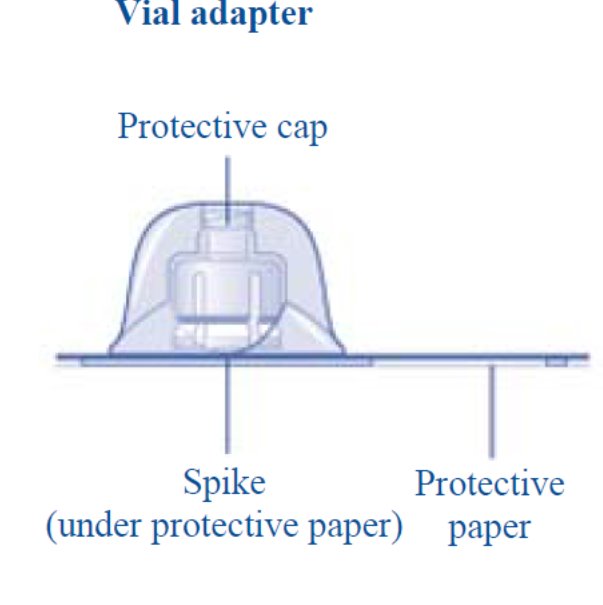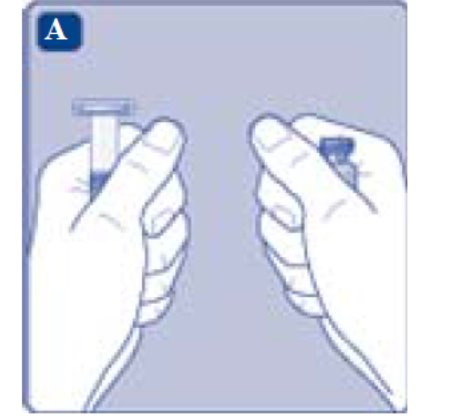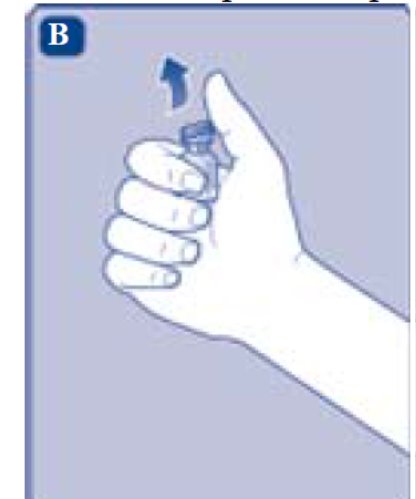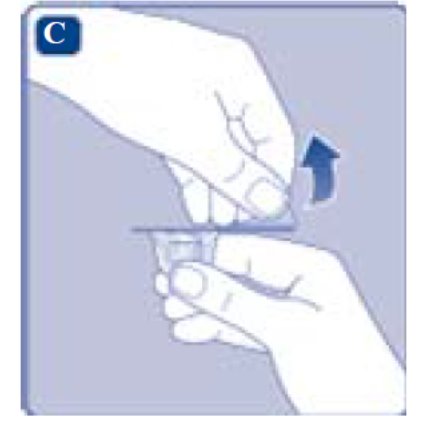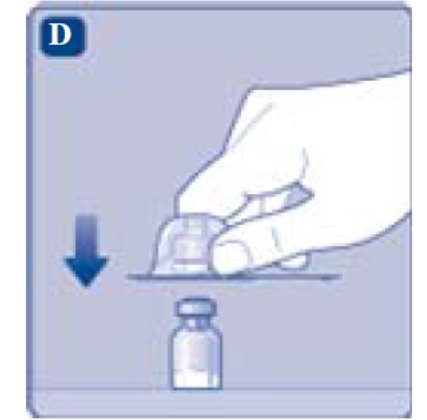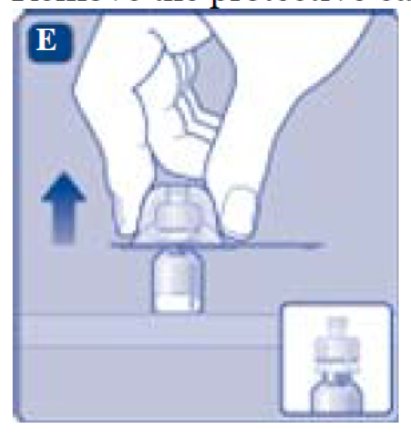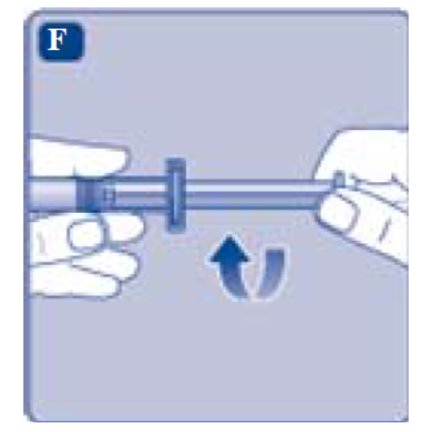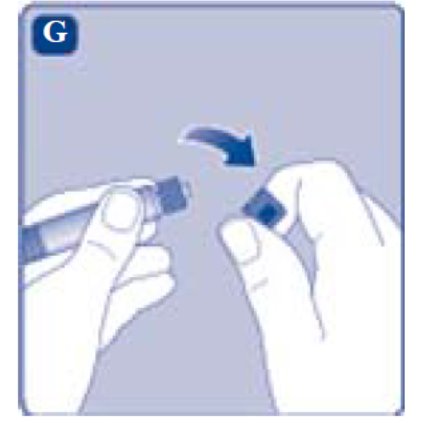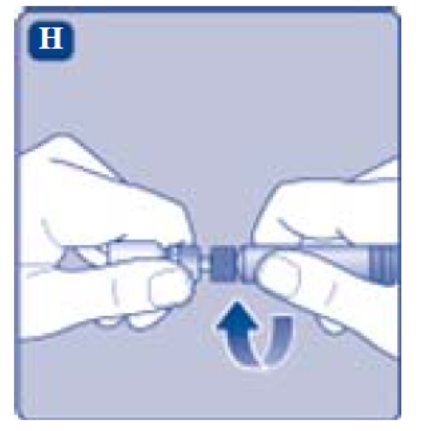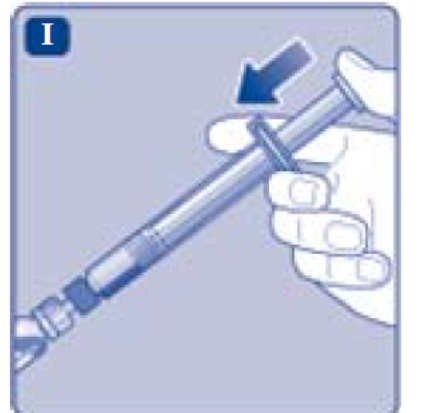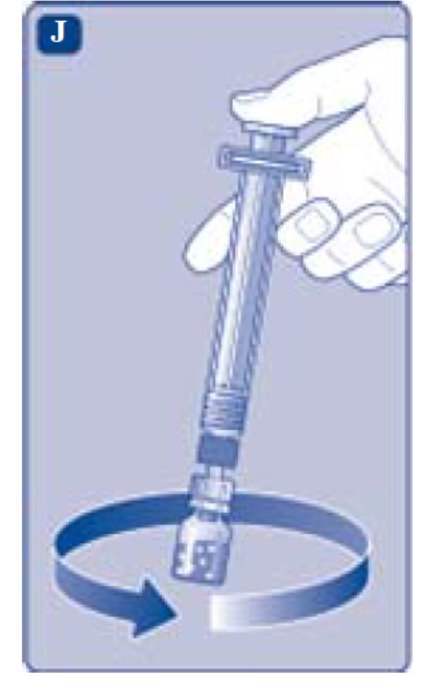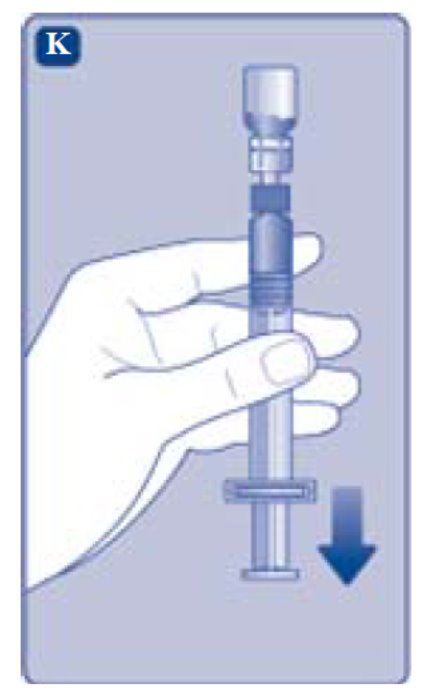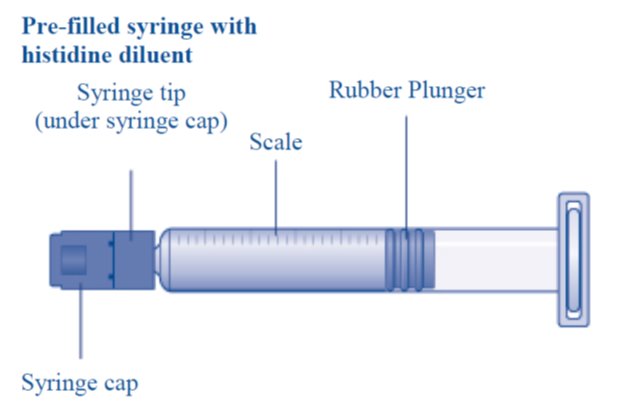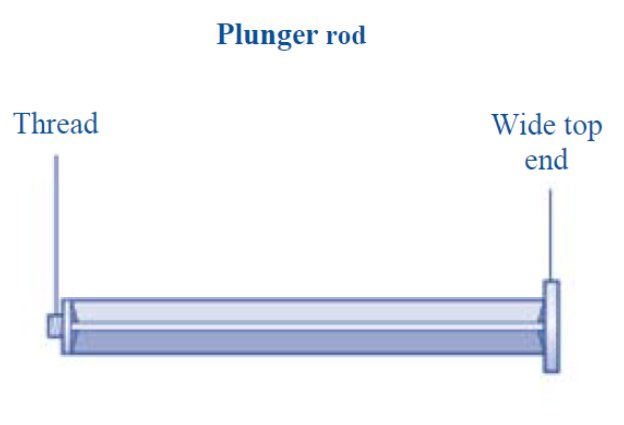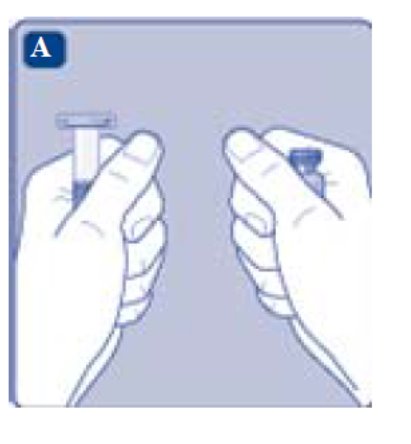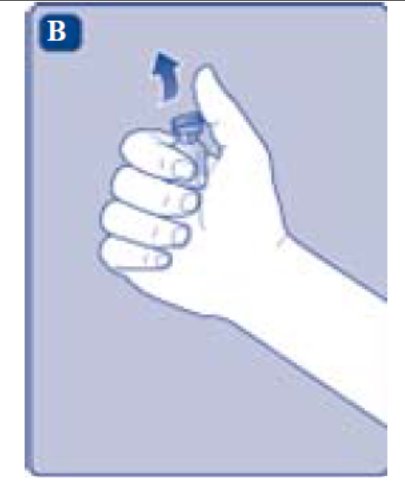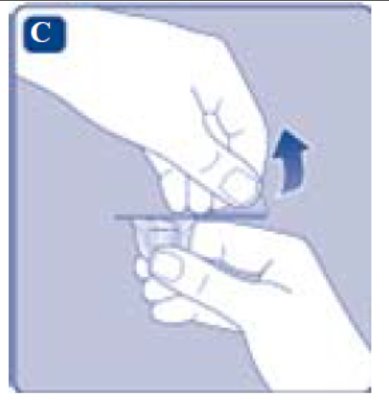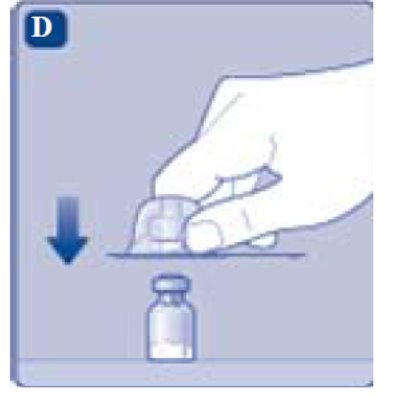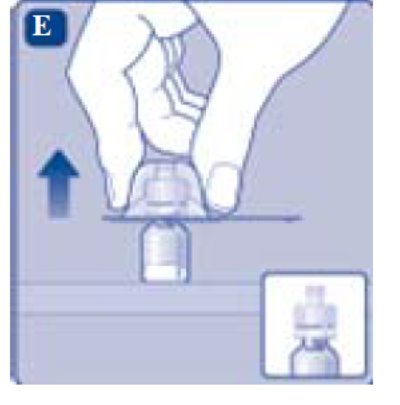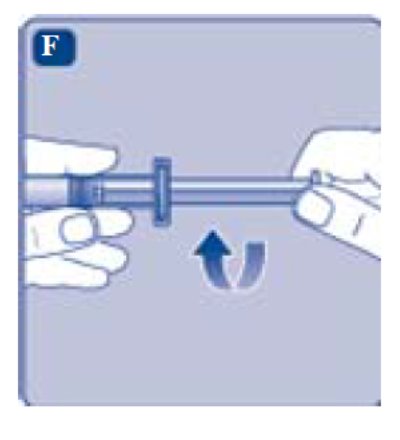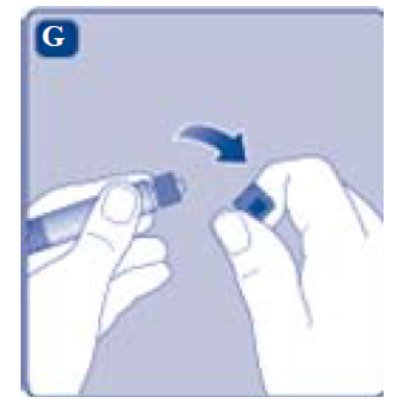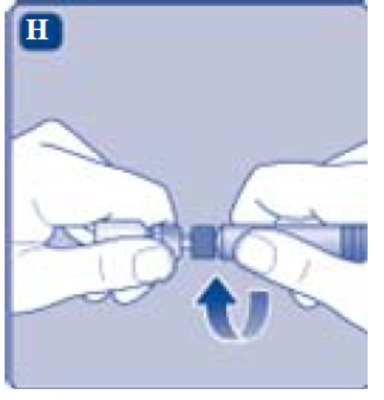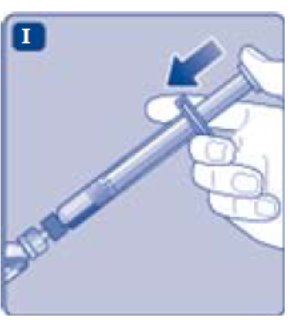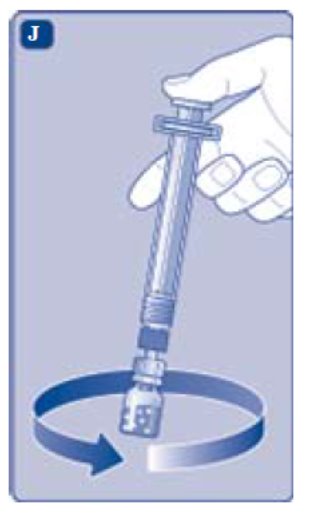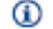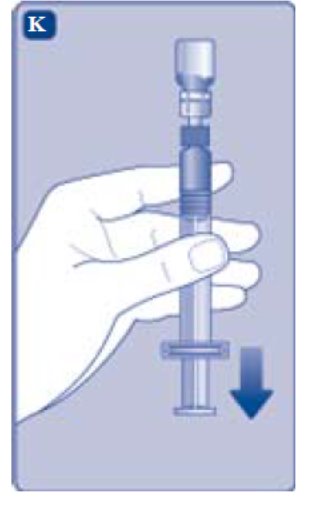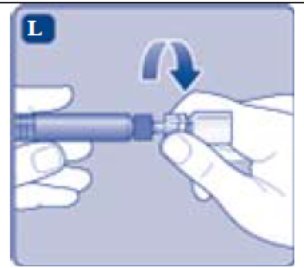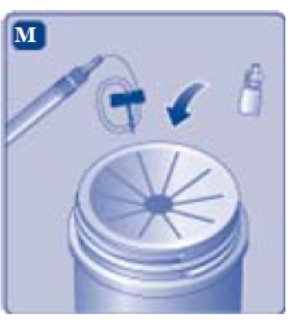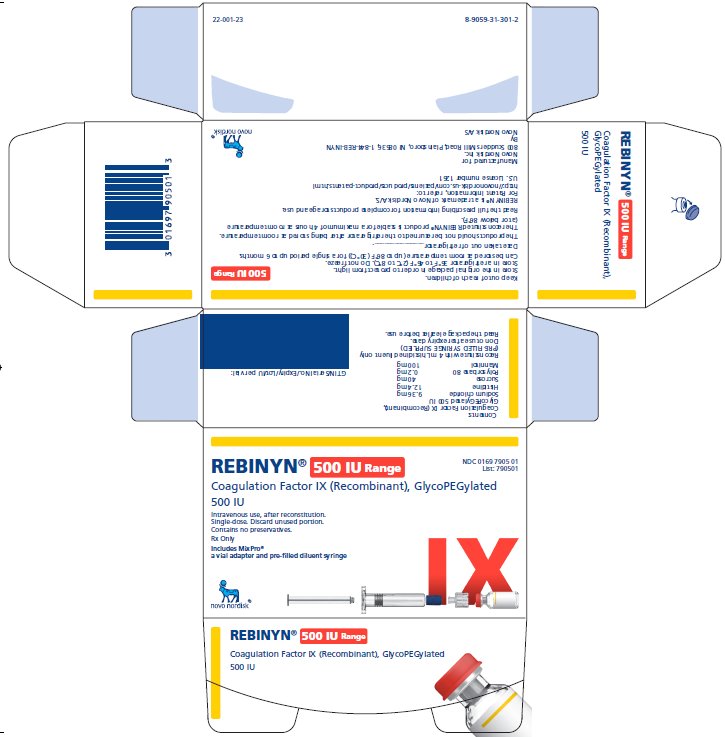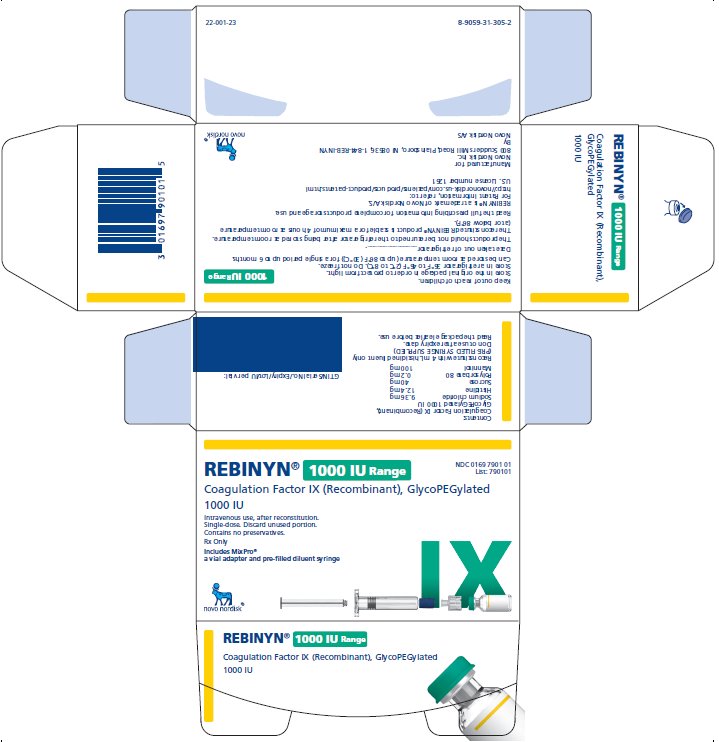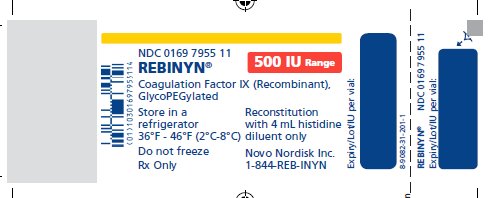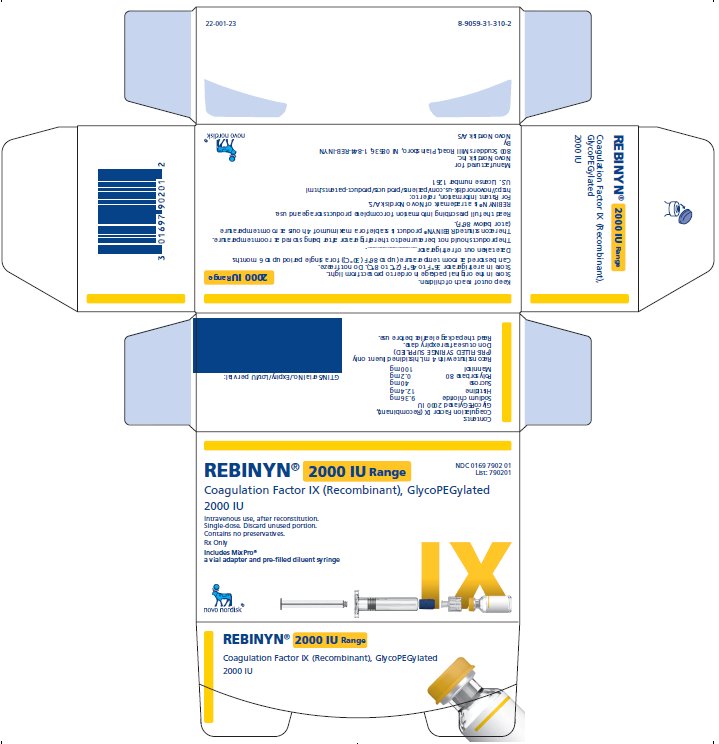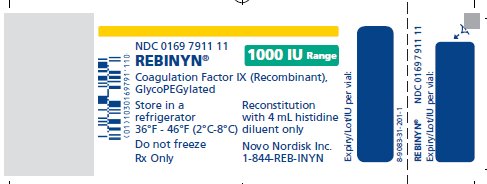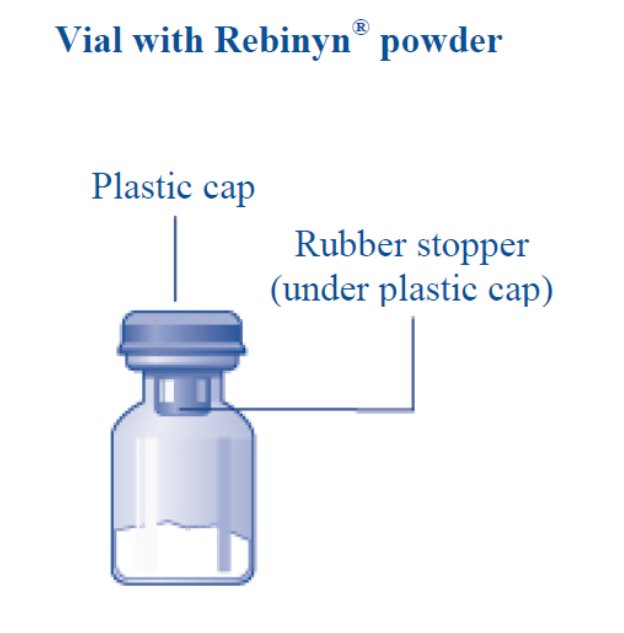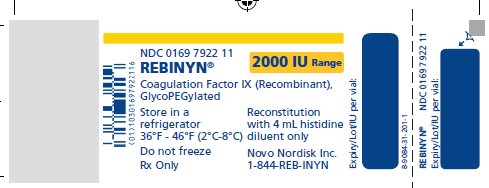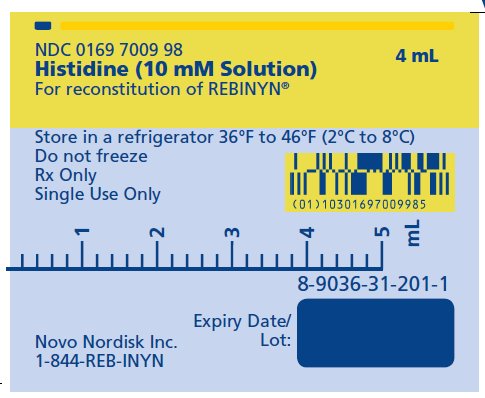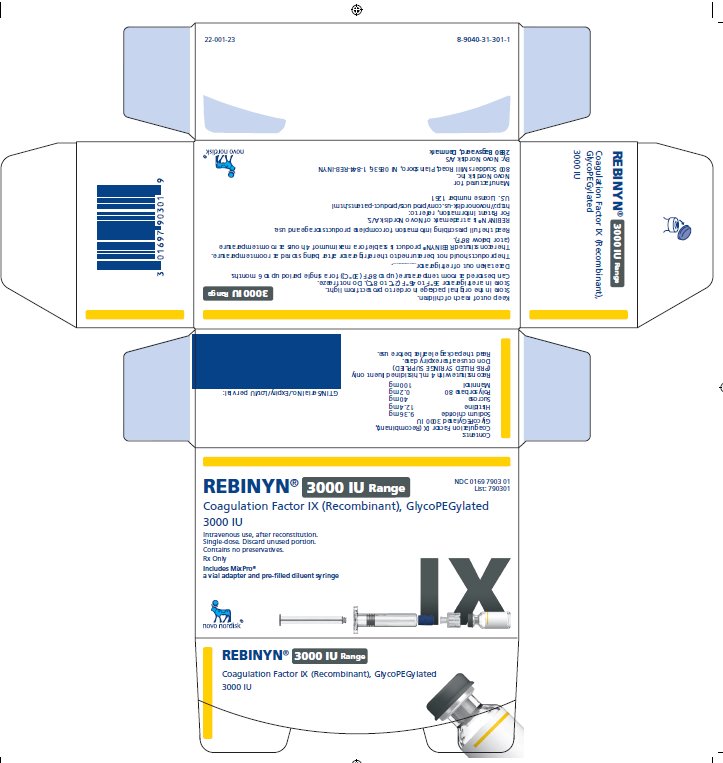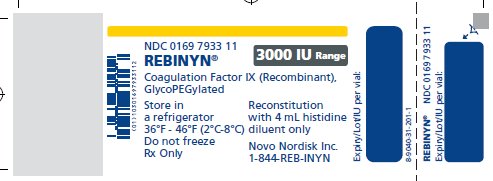 DRUG LABEL: REBINYN
NDC: 0169-7905 | Form: KIT | Route: INTRAVENOUS
Manufacturer: Novo Nordisk
Category: prescription | Type: HUMAN PRESCRIPTION DRUG LABEL
Date: 20220811

ACTIVE INGREDIENTS: COAGULATION FACTOR IX RECOMBINANT HUMAN 125 [iU]/1 mL
INACTIVE INGREDIENTS: SODIUM CHLORIDE 2.34 mg/1 mL; SUCROSE 10 mg/1 mL; MANNITOL 25 mg/1 mL; POLYSORBATE 80 0.05 mg/1 mL; HISTIDINE 3.10 mg/1 mL; HISTIDINE

HIGHLIGHTS OF PRESCRIBING INFORMATION

These highlights do not include all the information needed to use REBINYN safely and effectively. See full prescribing information for REBINYN.
REBINYN® (Coagulation Factor IX (Recombinant), GlycoPEGylated)
lyophilized powder for solution for intravenous injection
Initial U.S. Approval: 2017

RECENT MAJOR CHANGES

Indications and Usage (1) ………………………………………07/2022

Dosage and Administration (2.1)…………………………………07/2022

1 INDICATIONS AND USAGE

REBINYN, Coagulation Factor IX (Recombinant), GlycoPEGylated, is a recombinant DNA-derived coagulation Factor IX concentrate indicated for use in adults and children with hemophilia B (congenital Factor IX deficiency) for:

- On-demand treatment and control of bleeding episodes
- Perioperative management of bleeding
- Routine prophylaxis to reduce the frequency of bleeding episodes

Limitations of Use: REBINYN is not indicated for immune tolerance induction in patients with hemophilia B (1).

2 DOSAGE AND ADMINISTRATION

For intravenous infusion after reconstitution only (2).

- Each carton and vial label for REBINYN states the actual Factor IX potency in international units (IU) (2.1).
On-demand treatment and control of bleeding episodes:
- 40 IU/kg body weight for minor and moderate bleeds, and 80 IU/kg body weight for major bleeds. Additional doses of 40 IU/kg can be given (2.1).
Perioperative management:
- Pre-operative dose of 40 IU/kg body weight for minor surgery, and 80 IU/kg body weight for major surgery. As clinically needed for the perioperative management of bleeding, repeated doses of 40 IU/kg (in 1-3 day intervals) within the first week after major surgery may be administered.
- Frequency may be extended to once weekly after the first week until bleeding stops and healing is achieved (2.1).
Routine prophylaxis:
- 40 IU/kg body weight once weekly (2.1).

3 DOSAGE FORMS AND STRENGTHS

REBINYN is available as a lyophilized powder in single-dose vials of 500, 1000, 2000, and 3000 IU (3).

4 CONTRAINDICATIONS

Do not use in patients who have known hypersensitivity to REBINYN or its components, including hamster proteins (4).

5 WARNINGS AND PRECAUTIONS

- Hypersensitivity reactions, including anaphylaxis, have occurred. Should hypersensitivity reactions occur, discontinue REBINYN and administer appropriate treatment (5.1).
- Neutralizing antibodies (inhibitors) to Factor IX have occurred following administration of REBINYN. Perform an assay that measures Factor IX inhibitor concentration if bleeding is not controlled with the recommended dose of REBINYN or if plasma Factor IX activity level fails to increase as expected (5.2, 5.5).
- The use of Factor IX- products has been associated with the development of thromboembolic complications (5.3).
- Nephrotic syndrome has been reported following immune tolerance induction with Factor IX-containing products in hemophilia B patients with Factor IX inhibitors and a history of allergic reactions to Factor IX. (5.4)
- Factor IX activity assay results may vary with the type of activated partial thromboplastin time reagent used (5.5).

6 ADVERSE REACTIONS

The most frequently reported adverse reactions (≥ 1%) in previously treated patients (PTPs) and previously untreated patients (PUPs) were itching and injection site reactions (6).

Additional frequently reported adverse reactions (≥ 1%) in PUPs included rash, Factor IX inhibition, hypersensitivity, and anaphylactic reaction (6).

In animals administered repeat doses of REBINYN, accumulation of polyethylene-glycol (PEG) was observed in the choroid plexus, pituitary, circumventricular organs, and cranial motor neurons (8.4 and 13.2). The potential clinical implications of these animal findings are unknown (6.3).

To report SUSPECTED ADVERSE REACTIONS, contact Novo Nordisk Inc. at 1-877-668-6777 or FDA at 1-800-FDA-1088 or www.fda.gov/medwatch.

8 USE IN SPECIFIC POPULATIONS

Pediatric Use: No dose adjustment is needed (8.4).

FULL PRESCRIBING INFORMATION

1 INDICATIONS AND USAGE

REBINYN, Coagulation Factor IX (Recombinant), GlycoPEGylated, is a recombinant DNA-derived coagulation Factor IX concentrate indicated for use in adults and children with hemophilia B (congenital Factor IX deficiency) for:

- On-demand treatment and control of bleeding episodes
- Perioperative management of bleeding
- Routine prophylaxis to reduce the frequency of bleeding episodes

Limitations of Use: REBINYN is not indicated for immune tolerance induction in patients with hemophilia B.

2 DOSAGE AND ADMINISTRATION

For intravenous infusion after reconstitution only.

2.1 Dosing Guidelines

- Dose and duration of treatment depend on the location and extent of bleeding, and the patient’s clinical condition.
- If monitoring of Factor IX activity is performed, use a chromogenic assay or selected one-stage clotting assay validated for use with REBINYN [see Warnings and Precautions (5.5)].
- Each carton and vial label for REBINYN states the actual Factor IX potency in IU.

On-demand Treatment and Control of Bleeding Episodes

REBINYN dosing for on-demand treatment and control of bleeding episodes is provided in Table 1.

Table 1: Dosing for On-demand Treatment and Control of Bleeding Episodes

Type of bleeding | Recommended dose; IU/kg body weight | Additional information
Minor and moderate; For example: Uncomplicated joint bleeds, minor muscular bleeds, mucosal or subcutaneous bleeds | 40 | A single dose should be sufficient for minor and moderate bleeds. Additional doses of 40 IU/kg can be given.
Major; For example: Intracranial, retroperitoneal, iliopsoas and neck bleeds, muscle bleeds with compartment syndrome and bleeds associated with a significant decrease in the hemoglobin level | 80 | Additional doses of 40 IU/kg can be given.

Perioperative Management

REBINYN dosing for perioperative management is provided in Table 2.

Table 2: Dosing for Perioperative Management

Type of surgical procedure | Recommended dose; IU/kg body weight | Additional Information
Minor; For example: Implanting pumps in subcutaneous tissue, skin biopsies or simple dental procedures | 40 | A single pre-operative dose should be sufficient. Additional doses can be given if needed.
Major; For example: Body cavity is entered, mesenchymal barrier is crossed, fascial plane is opened, organ is removed, normal anatomy is operatively altered | 80 | Pre-operative dose
Major; For example: Body cavity is entered, mesenchymal barrier is crossed, fascial plane is opened, organ is removed, normal anatomy is operatively altered | 40 | As clinically needed for the perioperative management of bleeding, repeated doses of 40 IU/kg (in 1-3 day intervals) within the first week after major surgery may be administered.*; Due to the long half-life of REBINYN, the frequency of dosing in the post-surgical setting may be extended to once weekly after the first week until bleeding stops and healing is achieved.

*See 12.3 Pharmacokinetics, Table 8

Routine Prophylaxis

For prophylaxis use, the recommended dose is 40 IU/kg body weight once weekly.

Adjust dosing regimen based on individual patient’s bleeding pattern, and physical activity.

2.2 Reconstitution

- Always wash hands and ensure that the area is clean before performing the reconstitution procedures.
- Use aseptic technique during the reconstitution procedures.
- If the patient uses more than one vial of REBINYN per infusion, reconstitute each vial according to the following instructions.

Overview of REBINYN Package

The instructions below serve as a general guideline for reconstitution of REBINYN. For full instructions, refer to the FDA-approved patient information and Instructions for Use.

Reconstitution

1. Bring the REBINYN vial and the pre-filled diluent syringe to room temperature.

2. Remove the plastic cap from the REBINYN vial.

3. Wipe the rubber stopper on the vial with a sterile alcohol swab and allow it to dry prior to use.
4. Remove the protective paper from the vial adapter. Do not remove the vial adapter from the protective cap.

5. Place the vial on a flat and solid surface. While holding the protective cap, place the vial adapter over the REBINYN vial and press down firmly on the protective cap until the vial adapter spike penetrates the rubber stopper.

6. Remove the protective cap from the vial adapter.

7. Grasp the plunger rod as shown in the diagram. Attach the plunger rod to the syringe by holding the plunger rod by the wide top end. Turn the plunger rod clockwise into the rubber plunger inside the pre-filled diluent syringe until resistance is felt.

8. Break off the syringe cap from the pre-filled diluent syringe by snapping the perforation of the cap.

9. Connect the pre-filled diluent syringe to the vial adapter by turning it clockwise until it is secured.

10. Push the plunger rod to slowly inject all the diluent into the vial.

11. Without removing the syringe, gently swirl the REBINYN vial until all of the powder is dissolved.
12. Administer the REBINYN solution immediately [see Administration (2.3)]. If not used immediately after reconstitution, store the solution in the vial with the vial adapter and the syringe attached, at room temperature ≤ 86°F (30°C). Do not store for longer than 4 hours.

2.3 Administration

For intravenous infusion only.

- Accidental needle stick with a needle contaminated with blood can transmit infectious viruses including HIV (AIDS) and hepatitis. If a needle stick occurs, obtain immediate medical attention. Place needles in a sharps container after single use.
- Inspect the reconstituted REBINYN solution visually prior to administration [see Description (11)]. The solution should be clear and have no particles. Do not use if particulate matter or discoloration is observed.
- Do not administer REBINYN in the same tubing or container with other medicinal products.
1. Invert the REBINYN vial and slowly draw the solution into the syringe.

2. Detach the syringe from the vial adapter by turning the syringe counterclockwise.
3. Attach the syringe to the luer end of an infusion needle set.
4. Infuse the reconstituted REBINYN intravenously slowly over 1 to 4 minutes.
5. After infusion, safely dispose of the syringe with the infusion set, the vial with the vial adapter, any unused REBINYN, and other waste materials.

Caution: The pre-filled diluent syringe is made of glass with an internal tip diameter of 0.037 inches, and is compatible with a standard Luer-lock connector.

Some needleless connectors for intravenous catheters are incompatible with the glass diluent syringes (for example, certain connectors with an internal spike, such as Clave® /MicroClave®, InVision-Plus®, InVision-Plus CS®, Invision-Plus Junior®, Bionector®), and their use can damage the connector and affect administration. To administer REBINYN through incompatible needleless connectors, withdraw the reconstituted product into a standard 10 mL sterile Luer-lock plastic syringe.

If you encounter any problems with attaching the pre-filled histidine-diluent syringe to any Luer‐lock compatible device, please contact Novo Nordisk at (844) 303-4448.

3 DOSAGE FORMS AND STRENGTHS

REBINYN is available as a white to off-white lyophilized powder in single-dose vials containing nominally 500, 1000, 2000, or 3000 IU per vial. Each carton and vial label for REBINYN states the actual Factor IX potency in IU.

After reconstitution with 4 mL of histidine diluent, the reconstituted solution contains approximately 125, 250, 500, or 750 IU per mL of REBINYN respectively.

4 CONTRAINDICATIONS

REBINYN is contraindicated in patients who have known hypersensitivity to REBINYN or its components (including hamster proteins) [see Warnings and Precautions (5.1) and Description (11)]

5 WARNINGS AND PRECAUTIONS

5.1 Hypersensitivity Reactions

Allergic-type hypersensitivity reactions, including anaphylaxis, have occurred with REBINYN. The product may contain traces of hamster proteins which in some patients may cause allergic reactions. Signs of allergic reactions, which can progress to anaphylaxis, may include angioedema, chest tightness, difficulty breathing, wheezing, urticaria, and itching. Observe patients for signs and symptoms of acute hypersensitivity reactions, particularly during the early phases of exposure to the product. Discontinue use of REBINYN if allergic- or anaphylactic - type reactions occur, and initiate appropriate treatment.

5.2 Inhibitors

The formation of inhibitors (neutralizing antibodies) to Factor IX has occurred following REBINYN. If expected plasma factor IX activity levels are not attained, or if bleeding is not controlled as expected with the administered dose, perform an assay that measures Factor IX inhibitor concentration. Monitor all patients using clinical observations and laboratory tests for the development of inhibitors [see Warnings and Precautions (5.5)].

An association between the development of Factor IX inhibitors and allergic reactions has been reported. Evaluate patients experiencing allergic reactions for the presence of an inhibitor. Patients with Factor IX inhibitors may be at an increased risk of severe allergic reactions with subsequent exposure to Factor IX.

5.3 Thrombotic Events

The use of Factor IX-containing products has been associated with thromboembolic complications. Due to the potential risk of thromboembolic complications, monitor patients for early signs of thrombotic and consumptive coagulopathy when administering this product to patients with liver disease, post-operatively, to newborn infants, or to patients at risk of thrombosis or disseminated intravascular coagulation (DIC). In each of these situations, the benefit of treatment with REBINYN should be weighed against the risk of these complications.

5.4 Nephrotic Syndrome

Nephrotic syndrome has been reported following immune tolerance induction therapy with Factor IX products in hemophilia B patients with Factor IX inhibitors, often with a history of allergic reactions to Factor IX. The safety and efficacy of using REBINYN for immune tolerance induction have not been established.

5.5 Monitoring Laboratory Tests

If monitoring of Factor IX activity is performed, use a chromogenic assay or selected one-stage clotting assay validated for use with REBINYN [see Dosage and Administration (2)].

The one-stage clotting assay results can be significantly affected by the type of activated partial thromboplastin time (aPTT) reagent used, which can result in over- or under-estimation of Factor IX activity. Avoid the use of silica-based reagents, as some may overestimate the activity of REBINYN. If a validated one-stage clotting or chromogenic assay is not available locally, then use of a reference laboratory is recommended.

If bleeding is not controlled with the recommended dose of REBINYN, or if the expected Factor IX activity levels in plasma are not attained, then perform a Bethesda assay to determine if Factor IX inhibitors are present.

6 ADVERSE REACTIONS

Common adverse reactions (incidence ≥ 1%) in PTPs reported in clinical trials for REBINYN were itching and injection site reactions. Common adverse reactions (incidence ≥ 1%) in PUPs reported in clinical trials for REBINYN were rash, FIX inhibitors, hypersensitivity, itching, injection site reaction, and anaphylactic reaction.

6.1 Clinical Trials Experience

Because clinical trials are conducted under widely varying conditions, adverse reaction rates observed in the clinical trials of a drug cannot be directly compared to rates in clinical trials of another drug and may not reflect the rates observed in clinical practice.

Previously Treated Patients (PTPs)

In five multicenter, prospective, non-controlled, open-label clinical trials, 115 PTPs [0 to 6 years old: 12 subjects (10%); 7 to 12 years old: 13 subjects (11%); 13 to 17 years old: 18 subjects (16%); ≥18 years old: 72 subjects (63%)] received at least one dose of REBINYN as part of routine prophylaxis, on-demand treatment of bleeding episodes, perioperative management of major and minor surgery, or pharmacokinetic evaluation [see Clinical Studies (14)]. A PTP was defined as a subject with a history of at least 150 exposure days to other Factor IX products (adolescent/adult subjects) or 50 exposure days to other Factor IX products (pediatric subjects), and no history of inhibitors. A total of 15,167 injections were administered over a median of 733 days (range: 29- 2951 days), equivalent to 15,137 exposure days and 292 patient-years.

Adverse reactions in PTPs are listed in Table 3.

Table 3: Summary of Adverse Reactions in Previously Treated Patients

System Organ Class | Adverse Reaction | Number of subjects (%); N=115
General disorders and administration site conditions | Injection site reactions | 4 (4)
Immune system disorders | Hypersensitivity | 1 (1)
Skin and subcutaneous tissue disorders | Itching | 3 (3)

Previously Untreated Patients (PUPs)

In one multicenter, prospective, non-controlled, open-label clinical trial conducted in PUPs, 50 subjects (≤6 years of age) received at least one dose of REBINYN [see Clinical Studies (14)]. A PUP was defined as a subject previously untreated or exposed to FIX-containing products less than or equal to 3 exposure days (5 previous exposures to blood components was acceptable). A total of 6,737 injections were administered over a median of 996 days (range: 61- 2,233 days), equivalent to 6,709 exposure days and 142 patient-years.

Adverse reactions in PUPs are listed in Table 4.

Table 4: Summary of Adverse Reactions in Previously Untreated Patients

System Organ Class | Adverse Reaction | Number of subjects (%); N=50
Blood and lymphatic system disorders | Factor IX inhibition | 4 (8)
General disorders and administration site conditions | Injection site reaction | 1 (2)
Immune system disorders | Anaphylactic reaction; Hypersensitivty | 1 (2); 3 (6)
Skin and subcutaneous tissue disorders | Rash; Itching | 9 (18); 2 (4)

6.2 Immunogenicity

Subjects were monitored for inhibitory antibodies to factor IX prior to dosing, on a monthly basis for the first three months, every two months up to one year, every three months for an additional year, and then every 6 months until end of trial.

No inhibitors were reported in the clinical trials in previously treated patients.

In an ongoing trial in previously untreated patients, one anaphylactic reaction has occurred with development of a factor IX inhibitor following treatment with REBINYN. Inhibitor development and anaphylactic reactions are more likely to occur during the early phases of factor IX replacement therapy [see Warnings and Precautions (5.1, 5.2)].

The detection of antibody formation is highly dependent on the sensitivity and specificity of the assay. Additionally, the observed incidence of antibody (including neutralizing antibody) positivity in an assay may be influenced by several factors, including assay methodology, sample handling, timing of sample collection, concomitant medications, and underlying disease.

6.3 Neurologic Considerations

Animals administered repeat doses of REBINYN showed accumulation of PEG in the choroid plexus, pituitary, circumventricular organs, and cranial motor neurons [see Use in Specific Populations (8.4) and Animal Toxicology and/or Pharmacology (13.2)]. The potential clinical implications of these animal findings are unknown.

In the pediatric studies, 47 PUPs and 25 PTPs receiving routine prophylaxis with REBINYN at a weekly dose of 40 IU/kg were followed for central nervous system (CNS)-related ADRs for 6 and 8 years, respectively. The median duration of follow up of ADRs in the PUP and PTP studies were 2 and 7 years, respectively. Furthermore, neurological examinations were prospectively conducted in 44 PUPs and 17 PTPs with a median follow up of 2 years, and neurocognitive assessments were prospectively performed in 38 PUPs and 16 PTPs with a median follow up of 1 year.

Although no clear clinical implications of the animal findings are known and no clear clinical neurologic or neurocognitive safety signal has emerged, the physician should consider whether the patient is vulnerable to cognitive impairment, such as infants and children who have developing brains, and patients who are cognitively impaired. Factors such as duration of use, cumulative dose, age of the patient and co-morbidities that may increase risk of adverse neurologic and/or neurocognitive events should be considered when prescribing REBINYN. Report adverse neurocognitive and neurologic reactions.

6.4 Postmarketing Experience

The following adverse reactions have been identified during post-approval use of REBINYN. Because these reactions are reported voluntarily from a population of uncertain size, it is not always possible to reliably estimate their frequency or establish a causal relationship to drug exposure.

Blood and lymphatic system disorders: Factor IX inhibitor development.

8 USE IN SPECIFIC POPULATIONS

8.1 Pregnancy

Risk Summary

There are no data with REBINYN use in pregnant women to determine whether there is a drug-associated risk. Animal reproduction studies have not been conducted with REBINYN. It is unknown whether REBINYN can cause fetal harm when administered to a pregnant woman or can affect fertility. In the U.S. general population, the estimated background risk of major birth defect and miscarriage in clinically recognized pregnancies is 2-4% and 15-20%, respectively.

8.2 Lactation

Risk Summary

There is no information regarding the presence of REBINYN in human milk, the effect on the breastfed infant, and the effects on milk production. The developmental and health benefits of breastfeeding should be considered along with the mother’s clinical need for REBINYN and any potential adverse effects on the breastfed infant from REBINYN or from the underlying maternal condition.

8.4 Pediatric Use

Safety and efficacy of REBINYN were evaluated in four clinical trials that included 43 PTPs and in one clinical trial that included 50 pediatric PUPs [see Adverse Reactions (6) and Clinical Studies (14)]. Twelve of these subjects were ≤ 6 years of age; 13 subjects were 7 to 12 years of age; and 18 subjects were 13 to 17 years of age. Pharmacokinetic parameters were evaluated for 28 of the pediatric PTPs who were treated with REBINYN 40 IU/kg [see Clinical Pharmacology (12.3)].

Body weight-adjusted clearance was observed to be higher for pediatric subjects than for adult subjects. However, in clinical trials, no dose adjustment was needed in pediatric subjects who received a fixed dose of 40 IU/kg every week for routine prophylaxis.

Juvenile Animal Toxicity Data

A juvenile animal neurotoxicity study was conducted to evaluate the potential neurotoxicity of REBINYN when intravenously administered 120-1200 IU/kg/twice weekly in immature male rats from 3 to 13 weeks of age, followed by a 13-week treatment-free period. Accumulation of PEG was observed in the choroid plexus, pituitary, circumventricular organs, and the cranial motor neurons. PEG levels in these tissues increased with dose and dose duration (10 weeks) and remained detectable after the 13-week treatment-free period. Treatment-related PEG-positive vacuolated macrophages were observed in the pituitary. The accumulation of PEG was not associated with neurobehavioral changes, fertility, or functional effects.

8.5 Geriatric Use

Clinical studies of REBINYN did not include sufficient numbers of subjects age 65 and over to determine whether or not they respond differently than younger subjects.

Animals administered repeat doses of REBINYN showed accumulation of PEG in the choroid plexus, pituitary, circumventricular organs, and cranial motor neurons. [see Use in Specific Populations (8.4) and Animal Toxicology and/or Pharmacology (13.2)]. The potential clinical implications of these animal findings are unknown. No adverse neurologic effects of PEG have been reported in adults exposed to REBINYN during clinical trials, however, use in older adults with baseline cognitive dysfunction has not been fully evaluated [see Neurologic Considerations (6.3)].

11 DESCRIPTION

REBINYN is a sterile, non-pyrogenic, white to off-white lyophilized powder for reconstitution with the provided histidine diluent for intravenous infusion. After reconstitution, the solution appears as a clear and colorless to slightly yellow liquid, free from visible particles and contains the following excipients per mL: sodium chloride, 2.34 mg; histidine, 3.10 mg; sucrose, 10 mg; mannitol, 25 mg; polysorbate 80, 0.05 mg. REBINYN is available in single-dose vials containing the labeled amount of Factor IX activity, expressed in IU. Each vial contains nominally 500 IU, 1000 IU, 2000, or 3000 IU. REBINYN potency is assigned using an in vitro, activated partial thromboplastin time (aPTT)-based, one-stage clotting assay calibrated against the World Health Organization (WHO) international standard for Factor IX concentrates. REBINYN contains no preservatives.

REBINYN is a purified recombinant human Factor IX (rFIX) with a 40 kilodalton (kDa) polyethylene-glycol (PEG) conjugated to the protein. The 40 kDa PEG group is selectively attached to specific -N-linked glycans in the rFIX activation peptide, with mono-PEGylated rFIX as the predominant form of REBINYN. The rFIX protein in REBINYN consists of a gamma-carboxylated (Gla) domain, two EGF-like (epidermal growth factor) domains, an activation peptide (which is cleaved off upon activation), and a protease domain. Once activated, the resulting rFIX has structural and functional properties similar to those of endogenous activated Factor IX. The primary amino acid sequence in REBINYN is identical to the Thr148 allelic form of human plasma-derived Factor IX and consists of 415 amino acids. The average molecular weight of REBINYN is approximately 98 kDa and the molecular weight of the protein moiety alone is 56 kDa. The nominal specific activity of REBINYN is 144 IU/mg protein.

REBINYN is produced by recombinant DNA technology in Chinese Hamster Ovary (CHO) cells. No additives of human or animal origin are used in the cell culture, purification, conjugation, or formulation of REBINYN. The rFIX protein is purified by a series of chromatographic steps, including an affinity chromatography step using a monoclonal antibody (produced in CHO cells), to selectively isolate rFIX from the cell culture medium. The production process includes two dedicated viral clearance steps, namely a detergent treatment step for inactivation and a 20 nm filtration step for removal of viruses. The conjugation of the PEG-group is done by an enzymatic reaction during the purification process, followed by final purification of REBINYN.

12 CLINICAL PHARMACOLOGY

12.1 Mechanism of Action

Patients with hemophilia B are deficient in coagulation Factor IX, which is required for effective hemostasis. Treatment with REBINYN temporarily replaces the missing coagulation Factor IX.

The Factor IX in REBINYN is conjugated to a 40-kDa polyethylene glycol molecule, which slows down its removal from the blood circulation.

12.2 Pharmacodynamics

The administration of REBINYN increases plasma levels of Factor IX and can temporarily correct the coagulation defect in hemophilia B patients, as reflected by a decrease in aPTT.

12.3 Pharmacokinetics

Pharmacokinetic (PK) parameters of REBINYN were evaluated in previously treated subjects, including a subset of subjects in the adult/adolescent trial and all subjects in the main phase of the pediatric trial [see Clinical Studies (14)]. PK samples were collected prior to dosing and at multiple time points up to 168 hours after dosing. The analysis of plasma samples was conducted using the one-stage clotting assay.

Steady state pharmacokinetic parameters for adolescents and adults following once-weekly prophylactic treatment of REBINYN 40 IU/kg are shown in Table 5.

Table 5: Steady-state pharmacokinetic parameters of REBINYN (40 IU/kg) in adolescents and adults (geometric mean (CV))

PK Parameter | 13-17 years; N=3 | ≥ 18 years; N=6
Half-life (hours) | 103.1 (14.2) | 114.9 (9.7)
Incremental Recovery30min (IU/dL per IU/kg) | 1.82 (28.2) | 1.92 (19.6)
AUC0-168 (IU*hours/dL) | 9072 (22) | 9280 (15)
Clearance (mL/hour/kg) | 0.4 (16.7) | 0.4 (11.4)
Mean residence time (hours) | 144.4 (15.3) | 158.1 (9.6)
Vss (mL/kg) | 60.5 (31.1) | 65.8 (11.9)
Factor IX activity 168 h after dosing (%) | 28.9 (18.6) | 32.4 (17.1)

Abbreviations: AUC = area under plasma concentration-time curve; Vss= volume of distribution at steady state; CV=coefficient of variation.

The mean steady state pre-dose trough levels and post-dose peak levels across the clinical trials for all previously treated subjects are shown in Table 6.

Table 6: Factor IX peak and trough levels of REBINYN (40 IU/kg) by age at steady state

 | ≤ 6 years; N=12 | 7-12 years; N=13 | 13-17 years; N=9 | ≥18years N=20
Mean Factor IX peak level (%) (95% CI) | 65.5 (60.6; 70.7) | 71.4; (66.3; 77.0) | 82.8 (70.7; 96.9) | 97.9; (87.7; 109.3)
Mean Factor IX trough level* (%) (95% CI); Min, Max** | 15.4; (13.2; 17.9); 9.2; 24.5 | 18.7; (16.2; 21.6); 8.3; 28.3 | 23.7; (19.9; 28.2); 18.6; 34.6 | 29.3; (26.0; 33.0); 21.3; 42.2

* Factor IX activity from samples collected at clinical site visits just prior to administration of next weekly dose

**Individual geometric mean trough values

Single-dose pharmacokinetic parameters of REBINYN in children, adolescents and adults are listed in Table 7.

Table 7: Single Dose Pharmacokinetic Parameters of REBINYN (40 IU/kg) in children, adolescents and adults (geometric mean (CV))

PK Parameter | ≤ 6 years; N=12 | 7-12 years; N=13 | 13-17 years; N=3 | ≥18 years; N=6
Half-life (hours) | 69.6 (15.8) | 76.3 (25.5) | 89.4 (24.1) | 83.0 (22.5)
Incremental Recovery30min (IU/dL per IU/kg) | 1.51 (7.31) | 1.59 (16.2) | 1.96 (14.7) | 2.34 (11.3)
AUCinf (IU*h/dL) | 4617 (14) | 5618 (19) | 7986 (35) | 9063 (16)
Clearance (mL/hour/kg) | 0.8 (13.0) | 0.6 (21.9) | 0.5 (30.4) | 0.4 (14.7)
Mean residence time (hours) | 95.4 (15.3) | 105.1 (24.2) | 124.2 (24.4) | 115.5 (21.8)
Vss (mL/kg) | 72.3 (14.8) | 68.3 (21.7) | 58.6 (7.8) | 47.0 (15.9)
Factor IX activity 168 h after dosing (%) | 8.4 (16.3) | 10.9 (18.9) | 14.6 (59.6) | 16.8 (30.6)

Abbreviations: AUC = area under plasma concentration-time curve; Vss = volume of distribution at steady state; CV = coefficient of variation.

Pharmacokinetics were investigated in 9 subjects in the adult/adolescent trial, of which 5 were normal weight (body mass index (BMI) 18.5 to 24.9 kg/m^2) and 4 were overweight (BMI 25 to <29.9 kg/m^2). The pharmacokinetic parameters were not affected by BMI.

The Factor IX activity following 80 IU/kg infusion in major surgery is shown in Table 8.

Table 8: Factor IX activity following 80 IU/kg bolus for major surgery

 | 30 minutes | 8 hours^1 | 24 hours^1 | 48 hours^2
 | N=13 | N=12 | N=12 | N=7
Factor IX activity (%); Median; (Range) | 143; (123-224) | 138; (101-175) | 112; (62-146) | 73; (40-110)

^1 Excludes one subject with no Factor IX activity measurement obtained.

^2 Excludes two subjects with no Factor IX activity measurement obtained and additionally 4 subjects re-dosed prior to second day after surgery for whom the Factor IX activity at 24 hours were 84%, 112%, 131% and 134%. The 48 hours measurement reflects a measurement on the 2nd day after surgery (range 47-57 hours).

13 NONCLINICAL TOXICOLOGY

13.1 Carcinogenesis, Mutagenesis, Impairment of Fertility

Studies in animals to evaluate the carcinogenic or genotoxic potential of REBINYN, or dedicated studies to determine the effects of REBINYN on fertility, have not been performed. In a juvenile rat study (3 to 13 week old male rats), fertility was unaffected following 9 weeks of twice weekly administrations of up to 1200 IU/kg [see Use in Specific Populations (8.4)].

13.2 Animal Toxicology and/or Pharmacology

REBINYN was intravenously administered in repeat-dose toxicity studies in adult immune-deficient rats (40-1200 IU/kg/week for 26 weeks), immune-competent monkeys (350-3750 IU/kg/week for 4 weeks), and juvenile immune-competent rats (120‑1200 IU/kg/twice weekly for 10 weeks). Accumulation of PEG was detected in epithelial cells of the choroid plexus in the brain of the adult rats and monkeys. This finding was not associated with morphological changes or abnormal clinical signs. In juvenile rats, more comprehensive assessment of brain tissues demonstrated PEG accumulation in the choroid plexus, pituitary, circumventricular organs, and the cranial motor neurons [see Use in Specific Populations (8.4)].

14 CLINICAL STUDIES

Safety and efficacy of REBINYN was evaluated in five multicenter, non-controlled, open-label trials in on-demand treatment of bleeding episodes, perioperative management of major and minor surgery, and routine prophylaxis or pharmacokinetic evaluation in PTPs with hemophilia B (Factor IX activity ≤ 2%). The efficacy evaluation included 105 PTPs [62 adults (18 to 65 years old), 18 adolescents (13 to 17 years old), and 25 children (1 to 12 years old)].

- Adult/adolescent trial: The trial included 74 adolescent and adult subjects. There were two routine prophylaxis arms, with single-blind randomization to either 10 IU/kg or 40 IU/kg once-weekly for approximately 52 weeks, and an open-label on-demand treatment arm for approximately 28 weeks.
- Surgery trial: The surgery trial included 13 adolescent and adult subjects who received one infusion of REBINYN 80 IU/kg on the day of surgery, and post-operatively received infusions of 40 IU/kg, at the investigator’s discretion, for up to 3 weeks after surgery.
- Pediatric trial: The main phase of the pediatric trial included 25 PTPs (1 to 12 years old) in which subjects received routine prophylaxis with REBINYN 40 IU/kg once weekly for approximately 52 weeks until 50 EDs were reached.

Treatment of Bleeding Episodes

Previously Treated Patients

A total of 250 bleeding episodes were reported in 45 out of 69 PTPs receiving either REBINYN 40 IU/kg prophylaxis or on-demand treatment in the clinical program. Bleeding episodes were treated with REBINYN at 40 IU/kg for minor or moderate bleeds or 80 IU/kg for major bleeds, with additional doses of 40 IU/kg as needed. The median dose to treat a bleeding episode was 42 IU/kg.

An overall assessment of efficacy was performed by the subject (for home treatment) or the study site investigator (for treatment under medical supervision) using a 4-point scale of excellent, good, moderate, or poor. The overall success rate (defined as excellent or good) for treatment of bleeding episodes was 95% as shown in Table 9.

The success rate and dose needed for treatment of bleeding episodes were independent of the location of the bleeding. The success rate for treatment of bleeding episodes was also independent of whether the bleed was traumatic or spontaneous.

Table 9: Treatment of Bleeding Episodes in PTPs Receiving Either 40 IU/kg Prophylaxis or

On-Demand Treatment

Treatment | Prophylaxis with 40 IU/kg | On-Demand | Total
New Bleeding Episodes | 107 | 143 | 250
Efficacy assessment*
Excellent or Good | 101 (95%) | 135 (95%) | 236 (95%)
Moderate or Poor | 5 (5%) | 7 (5%) | 12 (5%)
Number of injections to treat a bleeding episode
1 injection | 100 (93%) | 120 (84%) | 220 (88%)
2 injections | 5 (5%) | 20 (14%) | 25 (10%)
>2 injections | 2 (2%) | 3 (2%) | 5 (2%)

*Efficacy assessment was based on 248 evaluated bleeding episodes (data missing for two bleeding episodes). Efficacy was assessed according to a four-point scale using:

Excellent: Abrupt pain relief and/or clear improvement in objective signs of bleeding within 8 hours after a single injection; Good: Noticeable pain relief and/or improvement in signs of bleeding within 8 hours after a single injection;

Moderate: Probable or slight beneficial effect within the first 8 hours after the first injection but requiring more than one injection within 8 hours;

Poor: No improvement, or worsening of symptoms within 8 hours after the second of two injections.

Perioperative Management

In the surgery trial, the efficacy analysis of REBINYN in perioperative management included 13 surgical procedures of which 9 were major and performed in 13 previously treated adolescent and adult patients. The procedures included 9 orthopedic, 1 gastrointestinal and 3 in the oral cavity.

The hemostatic effect during surgery was evaluated on a four-point scale of excellent, good, moderate, or poor. The intraoperative hemostatic effect was rated as excellent or good for the 13 surgeries, for a success rate of 100%. A pre-operative dose of 80 IU/kg REBINYN was effective, and no subjects required additional doses on the day of surgery. The median number of additional 40 IU/kg doses in the post-operative period was 2.0 for Days 1 to 6, 1.5 for Days 7-13, and 3.0 for Days 1 to 13. The mean total consumption of REBINYN in the pre- and post-operative period was 241 IU/kg (range: 81 to 460 IU/kg). There was no unexpected postoperative bleeding.

Three additional major surgeries and 18 minor surgery procedures were evaluated in the extension trial for REBINYN in previously treated patients. The hemostatic effect during major and minor surgery was confirmed with a success rate of 100%.

Routine Prophylaxis

Adult/Adolescent PTP Trial

In the main phase of the adult/adolescent PTP trial, 29 subjects (13 to 65 years old) received REBINYN 40 IU/kg once

weekly for approximately 52 weeks. The annualized bleeding rate for these subjects in the main phase is presented in Table 10. Eighteen of 20 (90%) target joints per ISTH definition (≥ 3 spontaneous bleeds into a single joint within a consecutive 6-month period) reported in 13 subjects in the 40 IU/kg once weekly arm at baseline were considered resolved at the end of the main phase.

Table 10: Annualized Bleeding Rate (ABR) in the Adult/Adolescent PTP Trial (40 IU/kg Once Weekly Arm) –

Main Phase

 | Main Phase
Age of patient | 13-17 years; N=9 | 18-65 years; N=20 | Overall; ≥ 13 years; N=29
Total ABR
Poisson-estimated mean (95% CI) | 2.19 (0.73 ; 6.54) | 2.68 (1.34 ; 5.35) | 2.52 (1.40; 4.52)
Median (Q1; Q3) | 1.93 (0.00 ; 4.01) | 1.03 (0.00 ; 4.01) | 1.04 (0.00; 4.01)
ABR for spontaneous bleeds
Poisson-estimated mean (95% CI) | 0.11 (0.00; 13.23) | 1.77 (0.77; 4.07) | 1.22 (0.46; 3.25)
Median (Q1; Q3) | 0.00 (0.00; 0.00) | 0.00 (0.00; 1.51) | 0.00 (0.00; 0.99)
ABR for traumatic bleeds
Poisson-estimated mean (95% CI) | 2.08 (0.98; 4.42) | 0.91 (0.41; 2.02) | 1.29 (0.74; 2.25)
Median (Q1; Q3) | 1.93 (0.00; 3.87) | 0.00 (0.00; 1.01) | 0.00 (0.00; 2.05)
ABR for joint bleeds
Poisson-estimated mean (95% CI) | 1.42 (0.36; 5.57) | 2.19 (1.02; 4.73) | 1.94 (0.97; 3.88)
Median (Q1; Q3) | 0.97 (0.00; 2.17) | 0.51 (0.00; 2.04) | 0.97 (0.00; 2.07)

CI = confidence interval; Q1 = first quartile; Q3 = third quartile.

Pediatric PTP Trial

In the main phase of the pediatric PTP trial, 25 subjects 0 to 12 years of age received routine prophylactic administration of REBINYN 40 IU/kg once weekly for 52 weeks. The patients were stratified into two age groups: 0 to 6 years and 7 to 12 years, with a least 10 subjects in each arm. Two target joints in 2 subjects in the 7 to 12 years age group at baseline were considered resolved during the main phase.

Table 11: Annualized Bleeding Rate (ABR) in the Pediatric PTP Trial - Main Phase

 | Main Phase
Age of patient | ≤ 6 years N=12 | 7-12 years N=13
Mean treatment period (years) | 0.93 | 1.01
Total ABR
Poisson-estimated mean (95% CI) | 0.90 (0.43 ; 1.89) | 2.06 (1.31 ; 3.24)
Median (Q1; Q3) | 0.00 (0.00 ; 1.98) | 2.00 (0.96 ; 3.00)
ABR for spontaneous bleeds
Poisson-estimated mean (95% CI) | 0.27 (0.06 ; 1.26) | 0.61 (0.24 ; 1.57)
Median (Q1; Q3) | 0.00 (0.00 ; 0.00) | 0.00 (0.00 ; 0.96)
ABR for traumatic bleeds
Poisson-estimated mean (95% CI) | 0.63 (0.28 ; 1.43) | 1.14 (0.65 ; 2.01)
Median (Q1; Q3) | 0.00 (0.00 ; 1.00) | 0.98 (0.00 ; 1.93)
ABR for joint bleeds
Poisson-estimated mean (95% CI) | 0.18 (0.04 ; 0.72) | 0.92 (0.52 ; 1.62)
Median (Q1; Q3) | 0.00 (0.00 ; 0.00) | 0.96 (0.00 ; 1.93)

CI = confidence interval; Q1 = first quartile; Q3 = third quartile.

16 HOW SUPPLIED/STORAGE AND HANDLING

How Supplied

- REBINYN is supplied in packages comprised of a single-dose vial containing nominally 500, 1000, 2000, or 3000 IU of Factor IX potency; a MixPro® pre-filled diluent syringe containing 10 mM histidine solution (1.6 mg/mL), and a sterile vial adapter with 25 micrometer filter, which serves as a needleless reconstitution device.
- The actual Factor IX potency in IU is stated on each REBINYN carton and vial.

Table 12: REBINYN Presentations

Presentation (Nominal Product Strength; IU) | Cap Color Indicator | Carton NDC Number | Components
500 | Red | NDC 0169 7905 01 | - REBINYN in single-dose vial [NDC 0169 7955 11] - Pre-filled histidine diluent in syringe, 4 mL [NDC 0169 7009 98] - Vial adapter
1000 | Green | NDC 0169 7901 01 | - REBINYN in single-dose vial [NDC 0169 7911 11] - Pre-filled histidine diluent in syringe, 4 mL [NDC 0169 7009 98] - Vial adapter
2000 | Yellow | NDC 0169 7902 01 | - REBINYN in single-dose vial [NDC 0169 7922 11] - Pre-filled histidine diluent in syringe, 4 mL [NDC 0169 7009 98] - Vial adapter
3000 | Dark Gray | NDC 0169 7903 01 | - REBINYN in single-dose vial [NDC 0169 7933 11] - Pre-filled histidine diluent in syringe, 4 mL [NDC 0169 7009 98] - Vial adapter

- The REBINYN vials are made of glass, closed with a chlorobutyl rubber stopper (not made with natural rubber latex), and sealed with an aluminum cap.
- The pre-filled diluent syringes are made of glass, with a siliconised bromobutyl rubber plunger (not made with rubber latex).
- The closed vials and pre-filled diluent syringes are equipped with a tamper-evident snap-off cap which is made of polypropylene.

Storage and Handling

- Store REBINYN in the original package in order to protect from light.
- Store REBINYN under refrigeration at a temperature of 36°F-46°F (2°C – 8°C) for up to 24 months from the date of manufacture until the expiration date stated on the label.
- REBINYN may be stored at room temperature not to exceed 86°F (30°C) for up to 6 months within the 24-month time period. Record the date when the product was removed from the refrigerator in the space provided on the outer carton. The total time of storage at room temperature should not exceed 6 months. Do not return the product to the refrigerator.
- Do not use REBINYN after the end of the 6-month period at room temperature storage, or after the expiration date stated on the vial, whichever occurs earlier.
- Do not freeze REBINYN.
- Use REBINYN within 4 hours after reconstitution when stored at room temperature. Store the reconstituted product in the vial.
- Discard any unused reconstituted product.

17 PATIENT COUNSELING INFORMATION

- Advise patients to read the FDA-approved patient labeling (Patient Information and Instructions for Use).
- Inform patients of the early signs of hypersensitivity reactions including rash, hives, itching, facial swelling, tightness of the chest and wheezing. Advise patients to discontinue use of the product and contact their healthcare provider if these symptoms occur.
- Advise patients to contact their healthcare provider for further treatment and/or assessment if they experience a lack of a clinical response to Factor IX therapy, as in some cases this may be a manifestation of an inhibitor.
- Advise patients to contact their healthcare provider if they experience any thrombotic complications.
- Advise patients to follow the recommendations regarding proper sharps disposal provided in the FDA-approved Instructions for Use.

Version: 4

License Number: 1261

REBINYN® and MixPro® are trademarks of Novo Nordisk A/S.

For Patent Information, refer to: http://novonordisk-us.com/patients/products/product-patents.html

Clave® and MicroClave® are registered trademarks of ICU Medical Inc.

InVision-Plus®, InVision-Plus CS®, Invision-Plus® Junior® are registered trademarks of RyMed Technologies, Inc.

Bionector® is a registered trademark of Vygon.

© 2022 Novo Nordisk

For information contact:

Novo Nordisk Inc.

800 Scudders Mill Road

Plainsboro, NJ 08536, USA

1-844-REB-INYN

Manufactured by:

Novo Nordisk A/S

Novo Allé, DK-2880 Bagsvaerd

Patient Package Insert

Patient Product Information

REBINYN (reh-bē-NINE)

Coagulation Factor IX (Recombinant), GlycoPEGylated

Read the Patient Product Information and the Instructions For Use that come with REBINYN before you start taking this medicine and each time you get a refill, as there may be new information.

This Patient Product Information does not take the place of talking with your healthcare provider about your medical condition or treatment. If you have questions about REBINYN after reading this information, ask your healthcare provider.

What is the most important information I need to know about REBINYN?

Do not attempt to do an infusion yourself unless you have been taught how by your healthcare provider or hemophilia treatment center.

You must carefully follow your healthcare provider's instructions regarding the dose and schedule for infusing REBINYN so that your treatment will work best for you.

What is REBINYN?

REBINYN is an injectable medicine used to replace clotting Factor IX that is missing in patients with hemophilia B. Hemophilia B is an inherited bleeding disorder in all age groups that prevents blood from clotting normally.

REBINYN is used to treat, prevent, or reduce the frequency (number) of bleeding episodes in people with hemophilia B.

Your healthcare provider may give you REBINYN when you have surgery.

Who should not use REBINYN?

You should not use REBINYN if you

- are allergic to Factor IX or any of the other ingredients of REBINYN
- if you are allergic to hamster proteins

If you are not sure, talk to your healthcare provider before using this medicine.

Tell your healthcare provider if you are pregnant or nursing because REBINYN might not be right for you.

What should I tell my healthcare provider before I use REBINYN?

You should tell your healthcare provider if you

- Have or have had any medical conditions.
- Take any medicines, including non-prescription medicines and dietary supplements.
- Are nursing. It is not known if REBINYN passes into breast milk or if it can harm your baby.
- Are pregnant or planning to become pregnant. It is not known if REBINYN may harm your unborn baby.
- Have been told that you have inhibitors to Factor IX (because REBINYN may not work for you).

How should I use REBINYN?

Treatment with REBINYN should be started by a healthcare provider who is experienced in the care of patients with hemophilia B.

REBINYN is given as an infusion into the vein.

You may infuse REBINYN at a hemophilia treatment center, at your healthcare provider's office or in your home. You should be trained on how to do infusions by your hemophilia treatment center or healthcare provider. Many people with hemophilia B learn to infuse the medicine by themselves or with the help of a family member.

Your healthcare provider will tell you how much REBINYN to use based on your weight, the severity of your hemophilia B, and where you are bleeding. Your dose will be calculated in international units, IU.

Call your healthcare provider right away if your bleeding does not stop after taking REBINYN.

If your bleeding is not adequately controlled, it could be due to the development of Factor IX inhibitors. This should be checked by your healthcare provider. You might need a higher dose of REBINYN or even a different product to control bleeding. Do not increase the total dose of REBINYN to control your bleeding without consulting your healthcare provider.

Use in children

REBINYN can be used in children. Your healthcare provider will decide the dose of REBINYN you will receive.

If you forget to use REBINYN

If you forget a dose, infuse the missed dose when you discover the mistake. Do not infuse a double dose to make up for a forgotten dose. Proceed with the next infusions as scheduled and speak to your healthcare provider if you have any questions or concerns.

If you stop using REBINYN

Do not stop using REBINYN without consulting your healthcare provider.

If you have any further questions on the use of this product, ask your healthcare provider.

What if I take too much REBINYN?

Always take REBINYN exactly as your healthcare provider has told you. You should check with your healthcare provider if you are not sure. If you infuse more REBINYN than recommended, tell your healthcare provider as soon as possible.

What are the possible side effects of REBINYN?

Common Side Effects Include:

- infusion site reaction (bruising, bleeding, swelling, pain, or redness)
- itching
- rash

Your body can also make antibodies called “inhibitors” against Factor IX, including REBINYN, which may stop REBINYN from working properly. Your healthcare provider may need to test your blood for inhibitors from time to time.

You could have an allergic reaction to coagulation Factor IX products. Call your healthcare provider right away or get emergency treatment right away if you get, for example, any of the following signs of an allergic reaction: hives, chest tightness, wheezing, difficulty breathing, and/or swelling of the face.

You may be at an increased risk of forming blood clots in your body, especially if you have risk factors for developing blood clots. Call your healthcare provider if you have chest pain, difficulty breathing, leg tenderness or swelling.

These are not all of the possible side effects from REBINYN. Ask your healthcare provider for more information. You are encouraged to report side effects to FDA at 1-800-FDA-1088.

Tell your healthcare provider about any side effect that bothers you or that does not go away.

What are the REBINYN dosage strengths?

REBINYN comes in four different dosage strengths. The actual number of international units (IU) of Factor IX in the vial will be imprinted on the label and on the box. The four different strengths are as follows:

Cap Color Indicator | Nominal Strength
Red | 500 IU per vial
Green | 1000 IU per vial
Yellow | 2000 IU per vial
Dark Gray | 3000 IU per vial

Always check the actual dosage strength printed on the label to make sure you are using the strength prescribed by your healthcare provider.

How should I store REBINYN?

Prior to Reconstitution (mixing the dry powder in the vial with the diluent):

Store in original package in order to protect from light. Do not freeze REBINYN.

REBINYN vials can be stored in the refrigerator (36-46°F [2°C – 8°C]) for up to 24 months until the expiration date, or at room temperature (up to 86°F [30°C]) for a single period not more than 6 months.

If you choose to store REBINYN at room temperature:

- Note the date that the product is removed from refrigeration on the box.
- The total time of storage at room temperature should not be more than 6 months. Do not return the product to the refrigerator.
- Do not use after 6 months from this date or the expiration date listed on the vial, whichever is earlier.

Do not use this medicine after the expiration date which is on the outer carton and the vial. The expiration date refers to the last day of that month.

After Reconstitution:

The reconstituted (the final product once the powder is mixed with the diluent) REBINYN should appear clear without visible particles.

The reconstituted REBINYN should be used immediately.

If you cannot use the reconstituted REBINYN immediately, it should be used within 4 hours when stored at or below 86ºF (30°C). Store the reconstituted product in the vial.

Keep this medicine out of the sight and out of reach of children.

What else should I know about REBINYN and hemophilia B?

Medicines are sometimes prescribed for purposes other than those listed here. Do not use REBINYN for a condition for which it is not prescribed. Do not share REBINYN with other people, even if they have the same symptoms that you have.

For more information about REBINYN, please call Novo Nordisk at 1-844-REB-INYN.

Revised: 08/2022

REBINYN® is a trademark of Novo Nordisk A/S.

For Patent Information, refer to:

http://novonordisk-us.com/products/product-patents.html

© 2022 Novo Nordisk

Manufactured by:

Novo Nordisk A/S

Novo Allé

DK-2880 Bagsværd, Denmark

For information about REBINYN contact:

Novo Nordisk Inc.

800 Scudders Mill Road

Plainsboro, NJ 08536, USA

Instructions on how to use REBINYN® MixPro®

READ THESE INSTRUCTIONS CAREFULLY BEFORE USING REBINYN.

REBINYN is supplied as a powder. Before infusion (administration) it must be mixed (reconstituted) with the liquid diluent supplied in the syringe. The liquid diluent is a histidine solution. The mixed REBINYN must be infused into your vein (intravenous infusion). The equipment in this package is designed to mix and infuse REBINYN.

You will also need an infusion set (tubing and butterfly needle), sterile alcohol swabs, gauze pads, and bandages.

Don’t use the equipment without proper training from your doctor or nurse.

Always wash your hands and ensure that the area around you is clean.

When you prepare and infuse medication directly into the veins, it is important to use a clean and germ free (aseptic) technique. Improper technique can introduce germs that can infect the blood.

Don’t open the equipment until you are ready to use it.

Don’t use the equipment if it has been dropped, or if it is damaged. Use a new package instead.

Don’t use the equipment if it is expired. Use a new package instead. The expiration date is printed on the outer carton and on the vial, the vial adapter and the pre-filled syringe.

Don’t use the equipment if you suspect it is contaminated. Use a new package instead.

Don’t dispose of any of the items until after you have infused the mixed solution.

The equipment is for single use only.

Single-dose container. Discard unused portion.

Content

The package contains:

• Vial with REBINYN powder

• Vial adapter

• Pre-filled syringe with diluent

• Plunger rod (placed under the syringe)

1. Prepare the vial and the syringe

- Take out the number of REBINYN® packages you need.
- Check the expiry date.
- Check the name, strength and color of the package, to make sure it contains the correct product.
- Wash your hands and dry them properly using a clean towel or air dry.
- Take the vial, the vial adapter and the pre-filled syringe out of the carton. Leave the plunger rod untouched in the carton.
- Bring the vial and the pre-filled syringe to room temperature. You can do this by holding them in your hands until they feel as warm as your hands.

- Remove the plastic cap from the vial. If the plastic cap is loose or missing, don’t use the vial.
- Wipe the rubber stopper with a sterile alcohol swab and allow it to air dry for a few seconds before use to ensure that it is as germ free as possible.
- Don’t touch the rubber stopper with your fingers as this can transfer germs.

2. Attach the vial adapter

- Remove the protective paper from the vial adapter.

Don’t take the vial adapter out of the protective cap with your fingers. If you touch the spike on the vial adapter germs from your fingers can be transferred.

If the protective paper is not fully sealed or if it is broken, don’t use the vial adapter.

- Place the vial on a flat and solid surface.
- Turn over the protective cap, and snap the vial adapter onto the vial.
Once attached, don’t remove the vial adapter from the vial.

- Lightly squeeze the protective cap with your thumb and index finger as shown. Remove the protective cap from the vial adapter.
Don’t lift the vial adapter from the vial when removing the protective cap.

3. Attach the plunger rod and the syringe

- Grasp the plunger rod by the wide top end and take it out of the carton. Don’t touch the sides or the thread of the plunger rod. If you touch the sides or the thread germs from your fingers can be transferred.
- Immediately connect the plunger rod to the syringe by turning it clockwise into the rubber plunger inside the pre-filled syringe until resistance is felt.

- Remove the syringe cap from the pre-filled syringe by bending it down until the perforation breaks.
Don’t touch the syringe tip under the syringe cap. If you touch the syringe tip germs from your fingers can be transferred.
If the syringe cap is loose or missing, don’t use the pre-filled syringe.

- Screw the pre-filled syringe securely onto the vial adapter until resistance is felt.

4. Mix the powder with the diluent

- Hold the pre-filled syringe slightly tilted with the vial pointing downwards.
- Push the plunger rod to inject all the diluent into the vial.

- Keep the plunger rod pressed down and swirl the vial gently until all the powder is dissolved.
Don’t shake the vial as this will cause foaming.
- Check the mixed solution. It must be clear and colorless. If you notice visible particles or discoloration, don’t use it. Use a new package instead.

REBINYN is recommended to be used immediately after it is mixed.

If you cannot use the mixed REBINYN solution immediately, it should be used within 4 hours when stored at room temperature at or below 86°F (30°C). Store the reconstituted product in the vial.

Do not freeze mixed REBINYN solution or store it in syringes.

Keep mixed REBINYN solution out of direct light.

If your dose requires more than one vial, repeat step A to J with additional vials, vial adapters and pre-filled syringes until you have reached your required dose.

- Keep the plunger rod pushed completely in.
- Turn the syringe with the vial upside down.
- Stop pushing the plunger rod and let it move back on its own while the mixed solution fills the syringe.
- Pull the plunger rod slightly downwards to draw the mixed solution into the syringe.
- In case you only need part of the entire vial, use the scale on the syringe to see how much mixed solution you withdraw, as instructed by your doctor or nurse.
- While holding the vial upside down, tap the syringe gently to let any air bubbles rise to the top.
- Push the plunger rod slowly until all air bubbles are gone.

- Unscrew the vial adapter with the vial.

Don’t touch the syringe tip. If you touch the syringe tip germs from your fingers can be transferred.

Caution: The pre-filled diluent syringe is made of glass with an internal tip diameter of 0.037 inches, and is compatible with a standard Luer-lock connector.

Some needleless connectors for intravenous catheters are incompatible with the glass diluent syringes (for example, certain connectors with an internal spike, such as Clave® /MicroClave®, InVision-Plus®, InVision-Plus CS®, Invision-Plus® Junior®, Bionector®).

The use of these needleless connectors can damage the connector and affect administration.

To administer REBINYN through incompatible needleless connectors, withdraw reconstituted product into a standard 10 mL sterile Luer-lock plastic syringe.

If you have encountered any problems with attaching the pre-filled histidine diluent syringe to any Luer‐lock compatible device, please contact Novo Nordisk at (844) 303-4448.

5. Infuse the mixed solution

REBINYN is now ready to infuse into your vein.

- Do not mix REBINYN with any other intravenous infusions or medications.
- Infuse the mixed solution slowly over 1 to 4 minutes as instructed by your doctor or nurse.

Infusing the solution via a central venous access device (CVAD) such as a central venous catheter or subcutaneous port:

- Use a clean and germ free (aseptic) technique. Follow the instructions for proper use for your connector and central venous access device in consultation with your doctor or nurse.
- Infusing into a CVAD may require using a sterile 10 mL plastic syringe for withdrawal of the mixed solution and infusion.
- If necessary, use 0.9% Sodium Chloride Injection, USP to flush the CVAD line before or after REBINYN infusion.
  The peel-off label found on the REBINYN vial can be used to record the lot number.

Disposal

- After infusion, safely dispose of all unused REBINYN solution, the syringe with the infusion set, the vial with the vial adapter, and other waste materials in an appropriate container for throwing away medical waste.
Don’t throw it out with the ordinary household trash.

Don’t disassemble the vial and vial adapter before disposal.

Don’t reuse the equipment.

Important information

Contact your healthcare provider or local hemophilia treatment center if you experience any problems.

For full Prescribing Information please read the other insert included in this package.

REBINYN® and MixPro® are trademarks of Novo Nordisk A/S.

For Patent Information, refer to: http://novonordisk-us.com/patients/products/product-patents.html

Clave® and MicroClave® are registered trademarks of ICU Medical Inc.

InVision-Plus®, InVision-Plus CS®, Invision-Plus®Junior® are registered trademarks of RyMed Technologies, Inc.

Bionector is a registered trademark of Vygon

© 2020 Novo Nordisk

Manufactured by:

Novo Nordisk A/S

DK-2880 Bagsvaerd, Denmark

For information about REBINYN contact:

Novo Nordisk Inc.

800 Scudders Mill Road

Plainsboro, NJ 08536, USA

License No: 1261

Revised: 06/2020

PRINCIPAL DISPLAY PANEL

NDC 0169 7905 01 List: 790501 500 IU Range

REBINYN®

(Coagulation Factor IX (Recombinant), GlycoPEGylated)

500 IU

Intravenous use, after reconstitution.

Single-dose. Discard unused portion.

Contains no preservatives.

Rx Only

Includes MixPro®

a vial adapter and pre-filled diluent syringe

Principal Display Panel

NDC 0169 7901 01 List: 790101 1000 IU Range

REBINYN®

(Coagulation Factor IX (Recombinant), GlycoPEGylated)

1000 IU

Intravenous use, after reconstitution.

Single-dose. Discard unused portion.

Contains no preservatives.

Rx Only

Includes MixPro®

a vial adapter and pre-filled diluent syringe

Principal Display Panel

NDC 0169 7902 01 List: 790201 2000 IU Range

REBINYN®

(Coagulation Factor IX (Recombinant), GlycoPEGylated)

2000 IU

Intravenous use, after reconstitution.

Single-dose. Discard unused portion.

Contains no preservatives.

Rx Only

Includes MixPro®

a vial adapter and pre-filled diluent syringe

NDC 0169 7955 11

REBINYN®

(Coagulation Factor IX (Recombinant), GlycoPEGylated)

500 IU

Store in a refrigerator 36°F - 46°F (2°C-8°C)

Do not freeze

Rx Only

Reconstitution with

4 mL histidine

diluent only

NDC 0169 7911 11

REBINYN®

(Coagulation Factor IX (Recombinant), GlycoPEGylated)

1000 IU

Store in a refrigerator 36°F - 46°F (2°C-8°C)

Do not freeze

Rx Only

Reconstitution with

4 mL histidine

diluent only

NDC 0169 7922 11

REBINYN®

(Coagulation Factor IX (Recombinant), GlycoPEGylated)

2000 IU

Store in a refrigerator 36°F - 46°F (2°C-8°C)

Do not freeze

Rx Only

Reconstitution with

4 mL histidine

diluent only

NDC 0169 7009 98

Histidine (10 mM Solution) 4 mL

For reconstitution of Tradename

Store in a refrigerator 36°F to 46°F (2°C to 8°C)

Do not freeze

Rx Only

Single Use Only

PACKAGE/LABEL PRINCIPAL DISPLAY PANEL

NDC 0169 7903 01

List: 790301

REBINYN®3000 IU Range

Coagulation Factor IX (Recombinant), GlycoPEGylated

3000 IU

Intravenous use, after reconstitution.

Single-dose. Discard unused portion.

Contains no preservatives.

Rx Only

Includes MixPro®

a vial adapter and pre-filled diluent syringe

NDC 0169 7933 11

REBINYN®3000 IU Range

Coagulation Factor IX (Recombinant), GlycoPEGylated

Store in a refrigerator

36°F - 46°F (2°C-8°C)

Do not freeze

Rx Only

Reconstitution with

4 mL histidine

diluent only